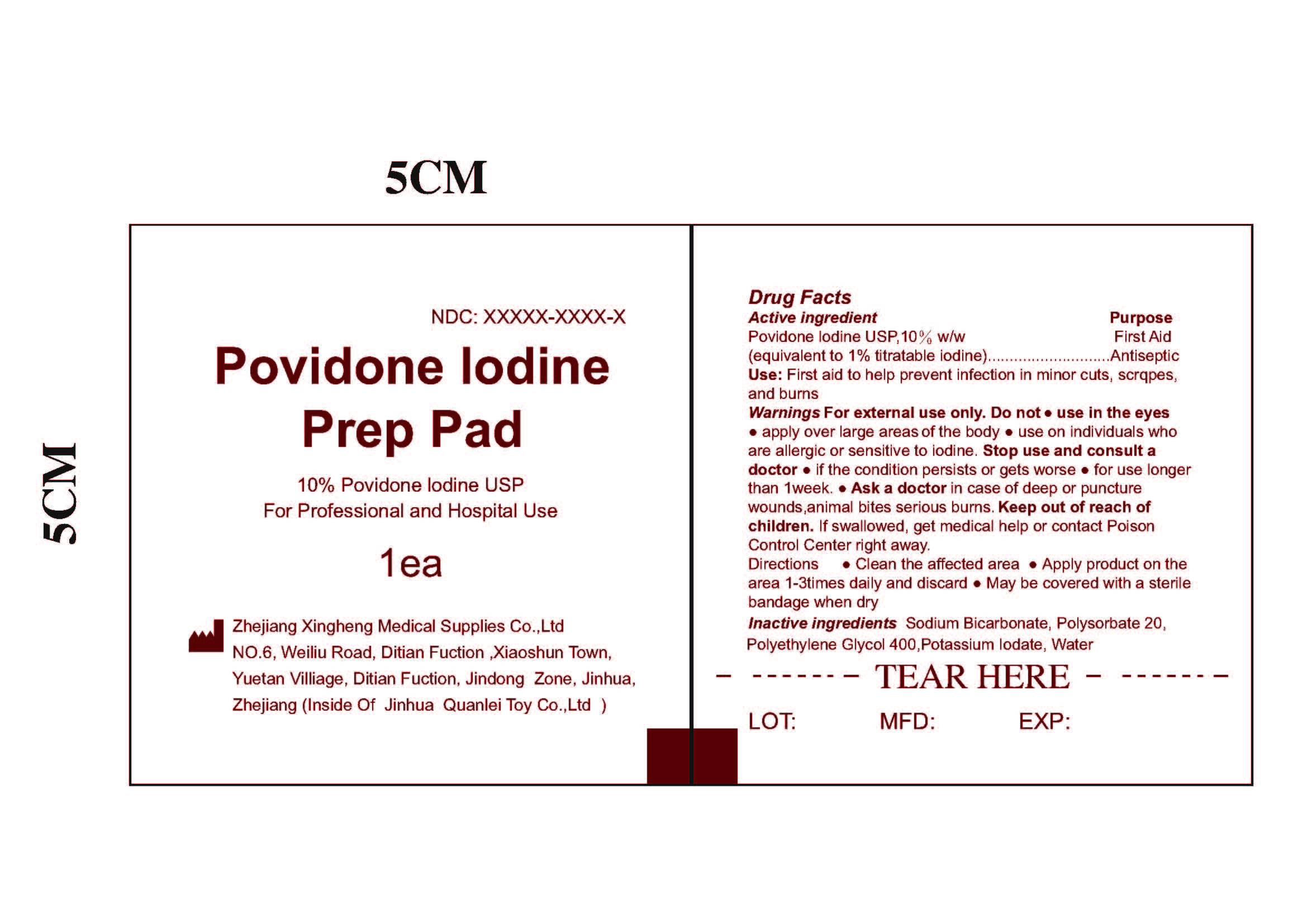 DRUG LABEL: Povidone-Iodine Prep Pad Medium Sterile
NDC: 81636-006 | Form: CLOTH
Manufacturer: Zhejiang Xingheng Medical Supplies Co., Ltd.
Category: otc | Type: HUMAN OTC DRUG LABEL
Date: 20220816

ACTIVE INGREDIENTS: POVIDONE-IODINE 10 g/100 g
INACTIVE INGREDIENTS: POLYETHYLENE GLYCOL 400 0.01 g/100 g; POTASSIUM IODATE 0.01 g/100 g; POLYSORBATE 20 0.01 g/100 g; SODIUM BICARBONATE 0.01 g/100 g; WATER 89.96 g/100 g

81636-006 Povidone-Iodine Pad

ACTIVE INGREDIENT

Povidone-lodine 10% w/w (equivalent to iodine 1%)

PURPOSE

Antiseptic

WARNINGS

For external use only.

WHEN USING

● Clean the affected area
● Apply product on the area 1-3times daily and discard
● May be covered with a sterile bandage when dry

Do not use:

- in the eyes.
- apply over large areas of the body.
- on individuals who are allergic or sensitive to iodine.

Stop use and consult a doctor

- if the condition persists or gets worse.
- for use longer than 1week.

Ask a doctor in case of deep or puncture wounds, animal bites & serious burns.

KEEP OUT OF REACH OF CHILDREN

If swallowed, get medical help or contact Poison Control Center right away.

INACTIVE INGREDIENT

Sodium Bicarbonate, Polysorbate 20, Polyethylene Glycol 400, Potassium Iodate, Water

DOSAGE AND ADMINISTRATION

Apply topically as needed to cleanse intendend area；
Apply the product to the skin, take the injection or puncture site as the center, slowly rotate from the inside to the outside, and gradually apply the product for two times, the disinfection area should be more than 5cmx5cm, and the action time should be1min.

INDICATIONS AND USAGE

Use for preparation of skin prior to injection，apply the product to the skin, take the injection or puncture site as the center, slowly rotate from the inside to the outside, and gradually apply the product for two times, the disinfection area should be more than 5cmx5cm, and the action time should be 1min.Please clean before disinfection.